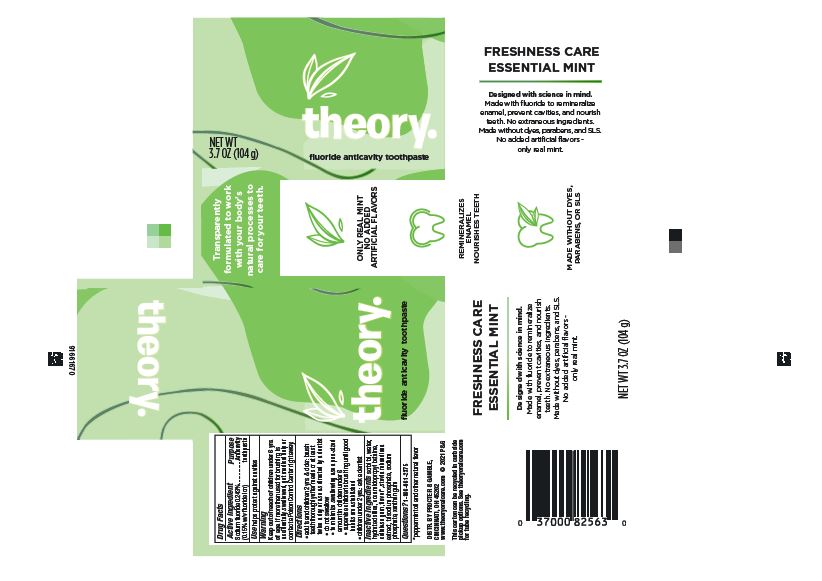 DRUG LABEL: Theory
NDC: 69423-919 | Form: PASTE, DENTIFRICE
Manufacturer: The Procter & Gamble Manufacturing Company
Category: otc | Type: HUMAN OTC DRUG LABEL
Date: 20250806

ACTIVE INGREDIENTS: SODIUM FLUORIDE 1.5 mg/1 g
INACTIVE INGREDIENTS: COCAMIDOPROPYL BETAINE; SORBITOL; WATER; HYDRATED SILICA; XANTHAN GUM; SODIUM PHOSPHATE; CARBOXYMETHYLCELLULOSE SODIUM; SODIUM PHOSPHATE, TRIBASIC, ANHYDROUS; STEVIA REBAUDIANA WHOLE

Theory Freshness Care Essential Mint

Drug Facts

Active ingredient

Sodium fluoride 0.243% (0.15% w/v fluoride ion)

Purpose

Anticavity toothpaste

Use

helps protect against cavities

Warnings

Keep out of reach of children under 6 yrs. of age.

WHEN USING

If more than used for brushing is accidentally swallowed, get medical help or contact a Poison Control Center right away.

Directions

- adults and children 2 yrs. & older: brush teeth thoroughly after meals or at least twice a day or use as directed by a dentist
  - do not swallow
  - to minimize swallowing use a pea-sized amount in children under 6
  - supervise children's brushing until good habits are established
- children under 2 yrs.: ask a dentist

Inactive ingredients

sorbitol, water, hydrated silica, cocamidopropyl betaine, cellulose gum, flavor*, stevia rebaudiana extract, trisodium phosphate, sodium phosphate, xanthan gum

Questions?

1-866-961-2375

PRINCIPAL DISPLAY PANEL - 104 g Tube Carton

NET WT 3.7 OZ (104 g)

theory.

fluoride anticavity toothpaste

FRESHNESS CARE

ESSENTIAL MINT

Designed with science in mind.
Made with fluoride to remineralize
enamel, prevent cavities, and nourish
teeth. No extraneous ingredients.
Made without dyes, parabens, and SLS.
No added artificial flavors -
only real mint.